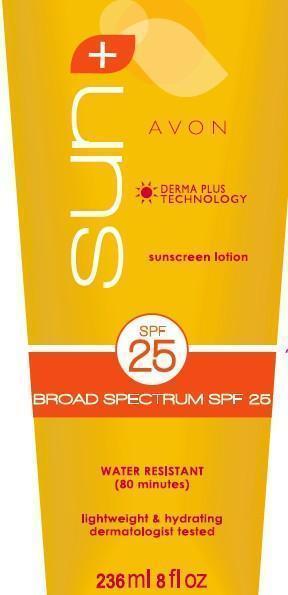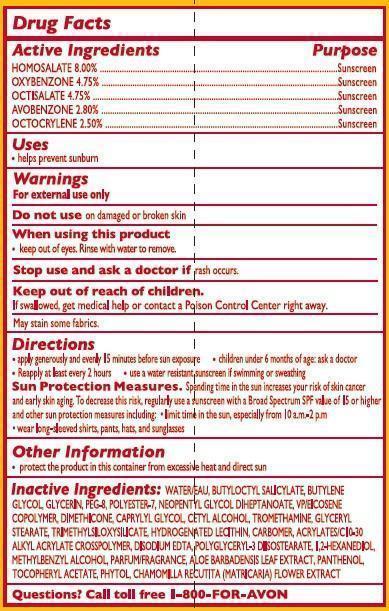 DRUG LABEL: Avon Sun
NDC: 10096-0295 | Form: LOTION
Manufacturer: New Avon LLC
Category: otc | Type: HUMAN OTC DRUG LABEL
Date: 20160217

ACTIVE INGREDIENTS: HOMOSALATE 80 mg/1 mL; OXYBENZONE 47.5 mg/1 mL; OCTISALATE 47.5 mg/1 mL; AVOBENZONE 28 mg/1 mL; OCTOCRYLENE 25 mg/1 mL

Active ingredients
HOMOSALATE 8.00%..................

OXYBENZONE 4.75%.....................

OCTISALATE 4.75%.....................

AVOBENZONE 2.80%...................

OCTOCRYLENE 2.50%..................

Purpose
.................................Sunscreen

.................................Sunscreen

.................................Sunscreen

.................................Sunscreen

.................................Sunscreen

Uses
• helps prevent sunburn

Warnings
For external use only

Do not use on damaged or broken skin

When using this product

- keep out of eyes. Rinse with water to remove.

Stop use and ask a doctor if rash occurs

Keep out of reach of children.

If swallowed, get medical help or contact a Poison Control Center right away.

Directions
• apply generously and evenly 15 minutes before sun exposure
• children under 6 months of age: ask a doctor

• reapply after 80 minutes of swimming or sweating
• immediately after towel drying

• at least every 2 hours

• Sun Protection Measures. Spending time in the sun increases your risk of skin cancer and early skin aging. To decrease this risk, regularly use a sunscreen with a Broad Spectrum SPF value of 15 or higher and other sun protection measures including:
• limit time in the sun, especially from 10 a.m. – 2 p.m.
• wear long-sleeved shirts, pants, hats, and sunglasses

Other information

• protect the product in this container from excessive heat and direct sun

Inactive Ingredients:
WATER/EAU, BUTYLOCTYL SALICYLATE, BUTYLENE GLYCOL, GLYCERIN, PEG-8, POLYESTER-7, NEOPENTYL GLYCOL DIHEPTANOATE, VP/EICOSENE COPOLYMER, DIMETHICONE, CAPRYLYL GLYCOL, CETYL ALCOHOL, TROMETHAMINE, GLYCERYL STEARATE, TRIMETHYLSILOXYSILICATE, HYDROGENATED LECITHIN, CARBOMER, ACRYLATES/C10-30 ALKYL ACRYLATE CROSSPOLYMER, DISODIUM EDTA,
POLYGLYCERYL-3 DIISOSTEARATE, 1,2-HEXANEDIOL, METHYLBENZYL ALCOHOL, PARFUM/FRAGRANCE, ALOE BARBADENSIS LEAF EXTRACT, PANTHENOL, TOCOPHERYL ACETATE, PHYTOL, CHAMOMILLA RECUTITA (MATRICARIA) FLOWER EXTRACT,

Questions?
Call toll free 1-800-FOR-AVON